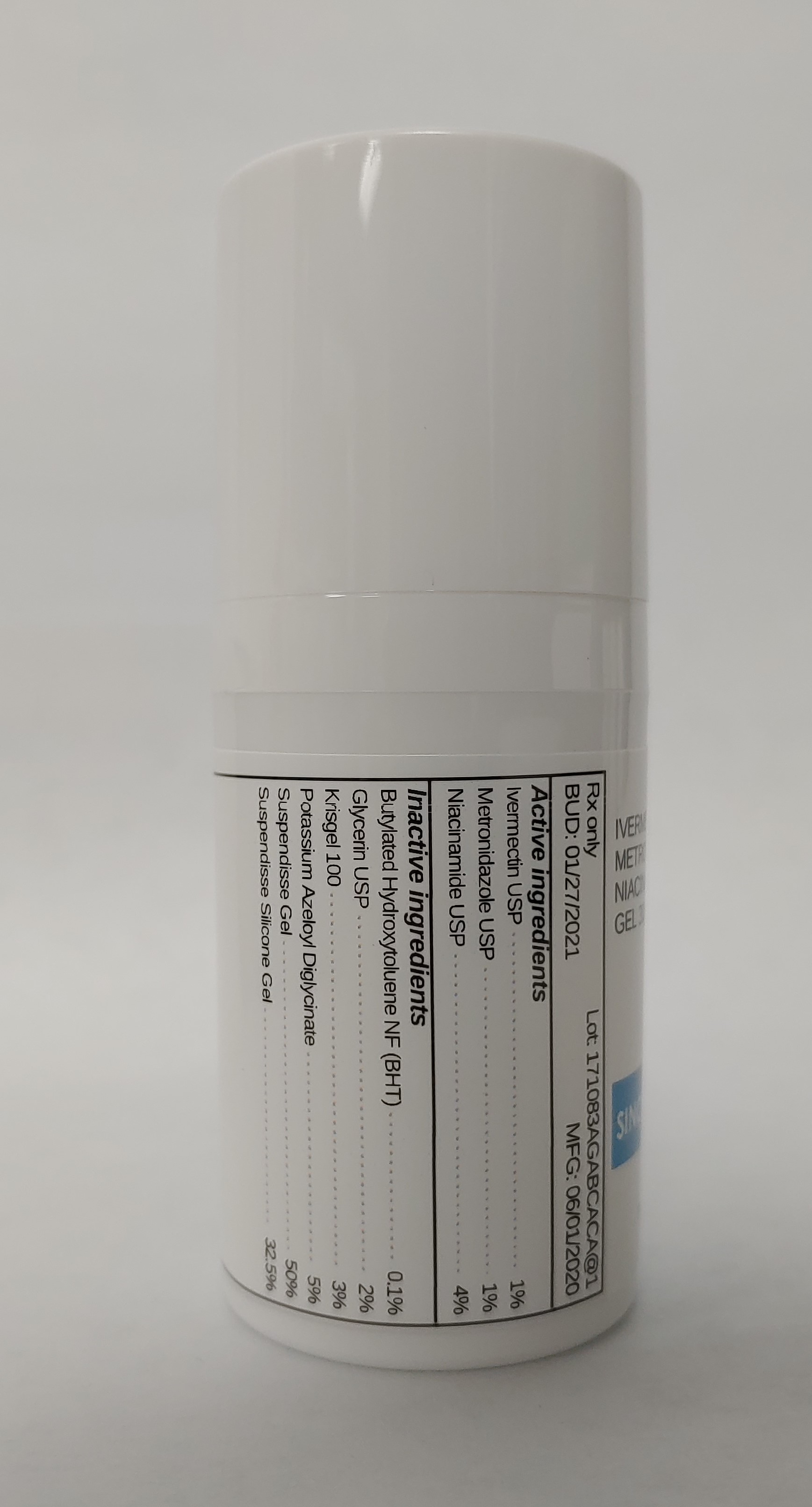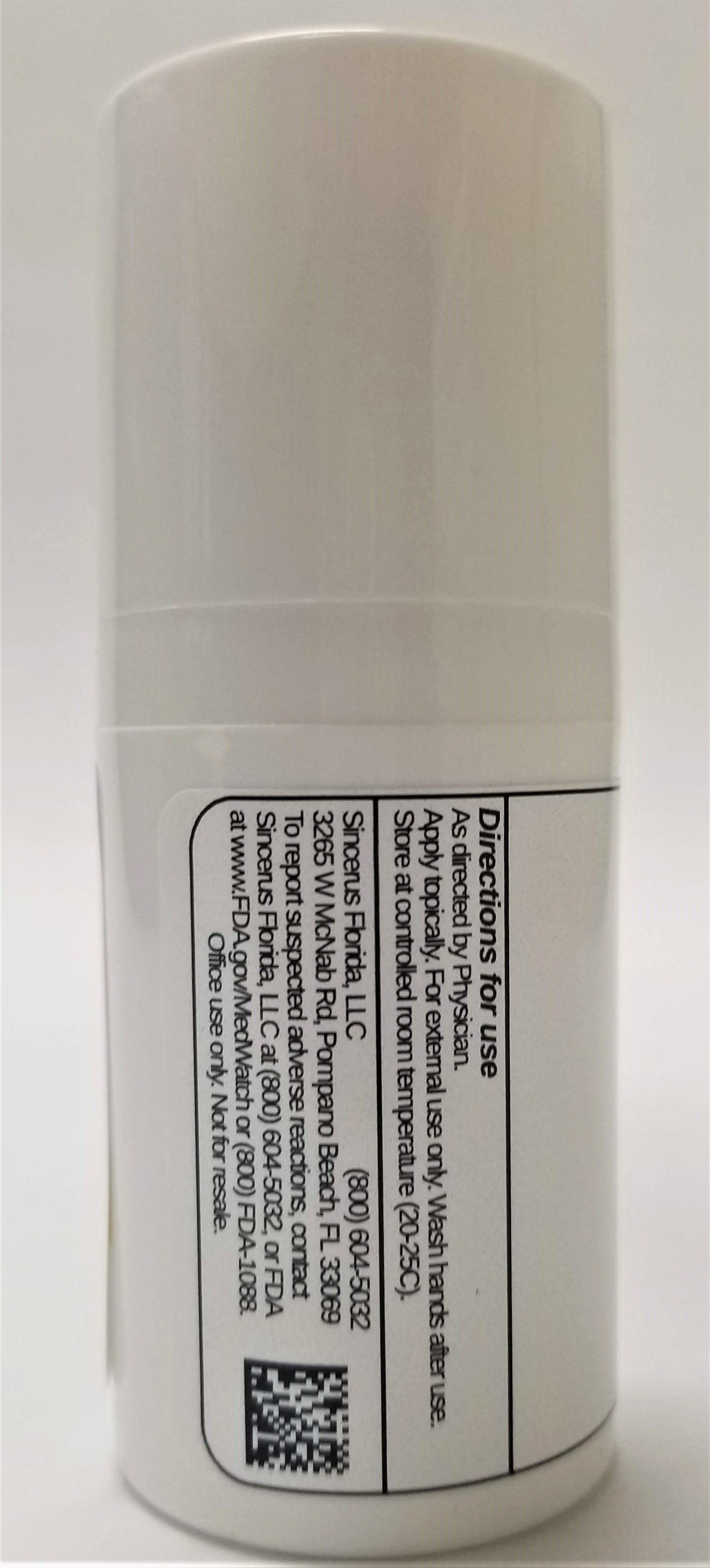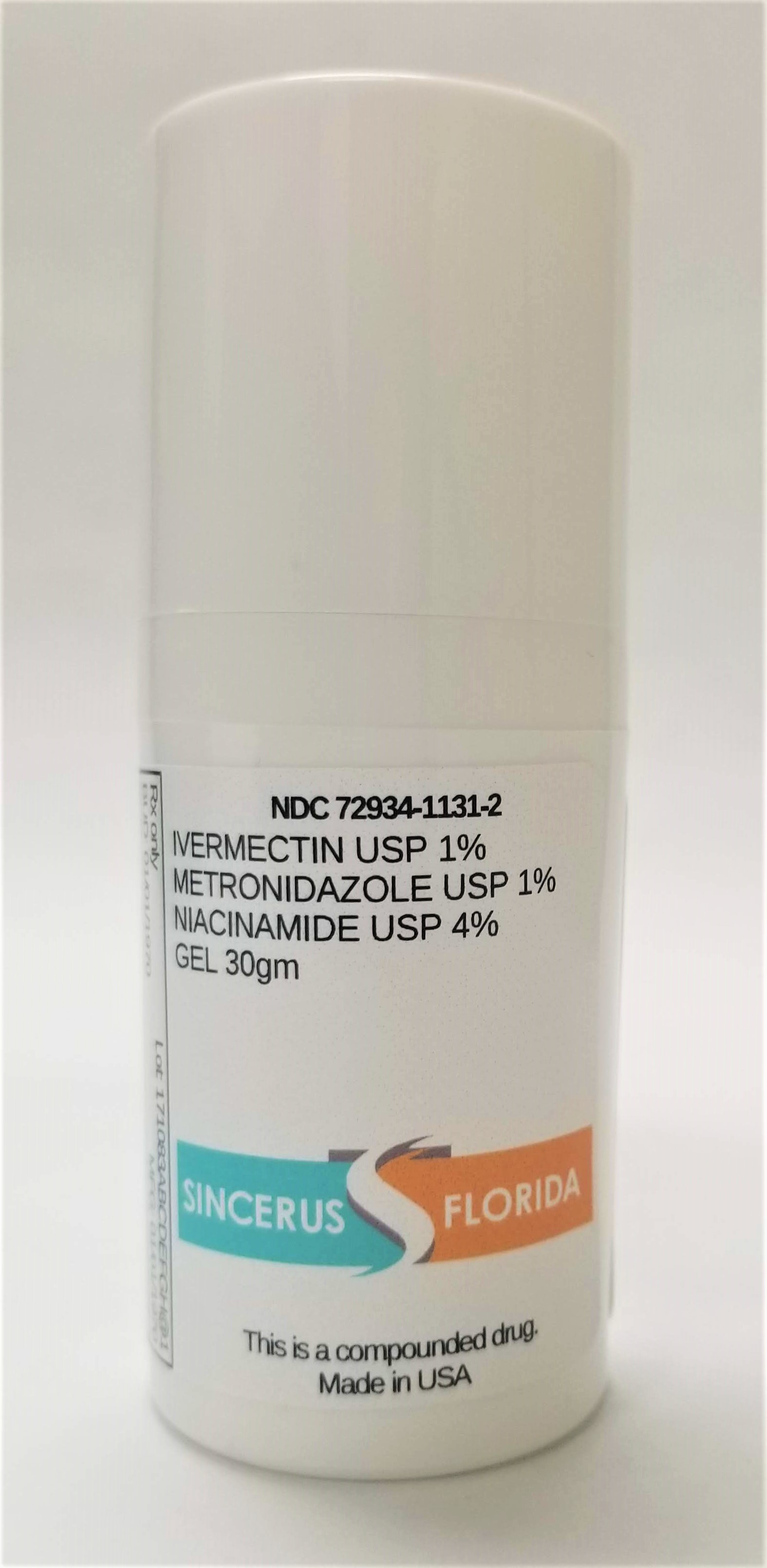 DRUG LABEL: IVERMECTIN 1% / METRONIDAZOLE 1% / NIACINAMIDE 4%
NDC: 72934-1131 | Form: GEL
Manufacturer: Sincerus Florida, LLC
Category: prescription | Type: HUMAN PRESCRIPTION DRUG LABEL
Date: 20200604

ACTIVE INGREDIENTS: METRONIDAZOLE 1 g/100 g; IVERMECTIN 1 g/100 g; NIACINAMIDE 4 g/100 g

IVERMECTIN 1% / METRONIDAZOLE 1% / NIACINAMIDE 4%